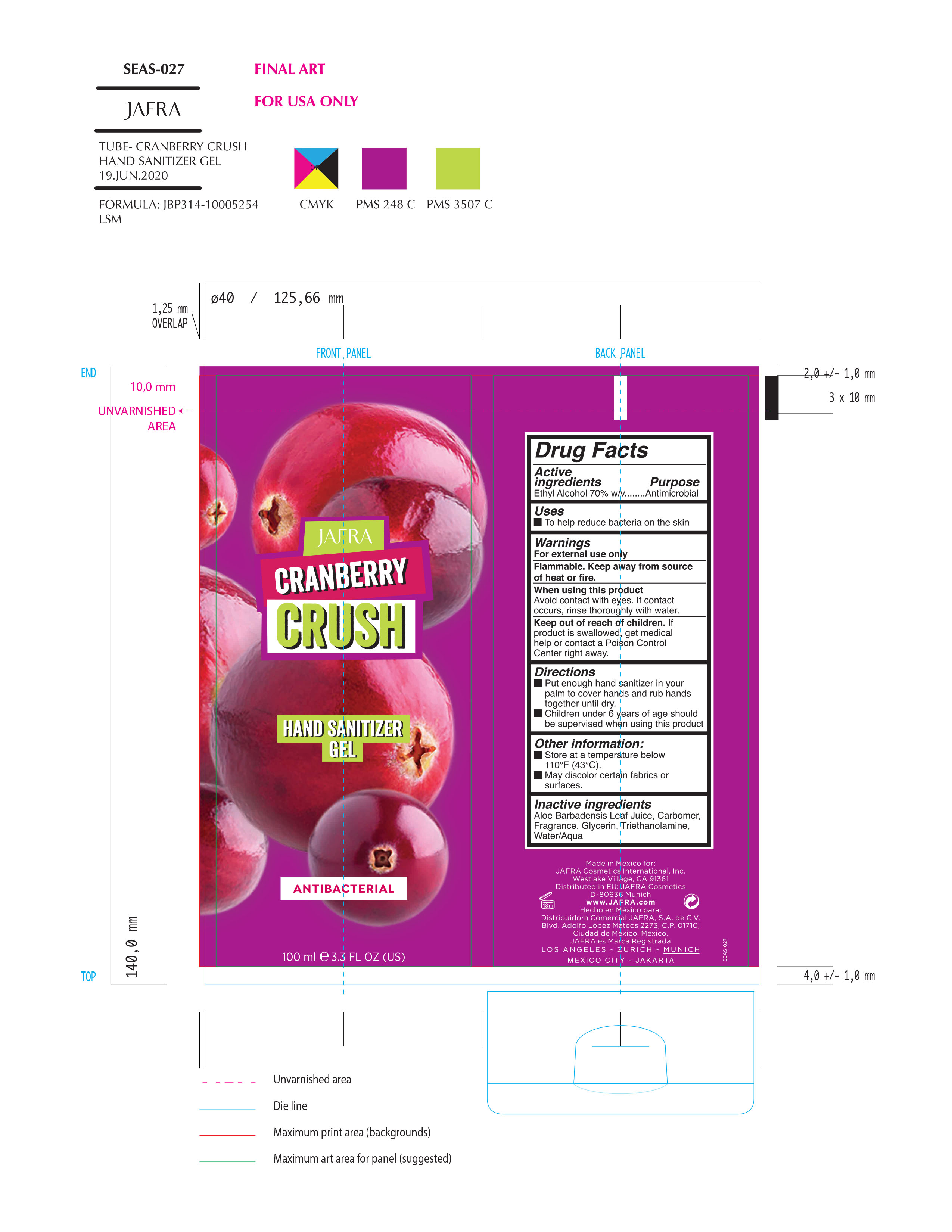 DRUG LABEL: Cranberry Crush Hand Sanitizer Gel
NDC: 68828-246 | Form: GEL
Manufacturer: Jafra cosmetics International
Category: otc | Type: HUMAN OTC DRUG LABEL
Date: 20200713

ACTIVE INGREDIENTS: ALCOHOL 70 mL/100 mL
INACTIVE INGREDIENTS: TROLAMINE; GLYCERIN; ALOE VERA LEAF; WATER; CARBOMER HOMOPOLYMER, UNSPECIFIED TYPE

Cranberry Crush Hand Sanitizer Gel

Active Ingredient(s)

Ethyl Alcohol 70% w/v. Purpose: Antimicrobial

Uses

To help reduce bacteria on the skin

When using this product keep out of eyes. If contact occurs, rinse thoroughly with water.

Warnings

For external use only. Flammable. Keep away from heat or flame

Keep out of reach of children. If swallowed, get medical help or contact a Poison Control Center right away.

Directions

- Put enough hand sanitizer in your palm to cover hands and rub hands together until dry.
- Children under 6 years of age should be supervised when using this product.

Other information

- Store at a temperature below 110F (43C)
- May discolor certain fabrics or surfaces

Inactive ingredients

Aloe Barbadensis Leaf Juice, Carbomer, Fragrance, Glycerin, Triethanolamine, Water/Aqua

Package Label - Principal Display Panel

Jafra Cranberry Crush

Hand Santizer Gel

Antibacterial

100ml 3.3 fl oz(US)